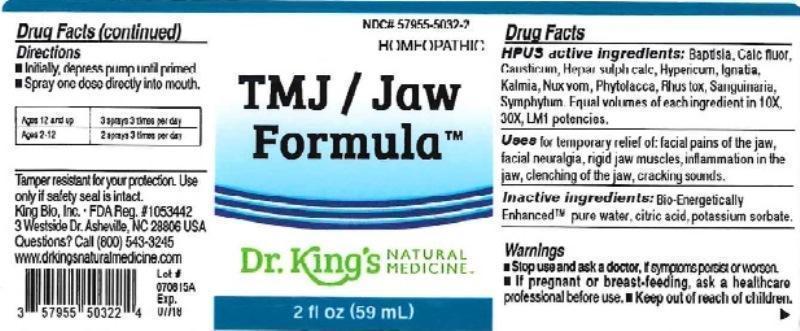 DRUG LABEL: TMJ / Jaw Formula
NDC: 57955-5032 | Form: LIQUID
Manufacturer: King Bio Inc.
Category: homeopathic | Type: HUMAN OTC DRUG LABEL
Date: 20160321

ACTIVE INGREDIENTS: BAPTISIA TINCTORIA ROOT 10 [hp_X]/59 mL; CALCIUM FLUORIDE 10 [hp_X]/59 mL; CAUSTICUM 10 [hp_X]/59 mL; CALCIUM SULFIDE 10 [hp_X]/59 mL; HYPERICUM PERFORATUM 10 [hp_X]/59 mL; STRYCHNOS IGNATII SEED 10 [hp_X]/59 mL; KALMIA LATIFOLIA LEAF 10 [hp_X]/59 mL; STRYCHNOS NUX-VOMICA SEED 10 [hp_X]/59 mL; PHYTOLACCA AMERICANA ROOT 10 [hp_X]/59 mL; TOXICODENDRON PUBESCENS LEAF 10 [hp_X]/59 mL; SANGUINARIA CANADENSIS ROOT 10 [hp_X]/59 mL; COMFREY ROOT 10 [hp_X]/59 mL
INACTIVE INGREDIENTS: WATER; ANHYDROUS CITRIC ACID; POTASSIUM SORBATE

TMJ / Jaw Formula™

ACTIVE INGREDIENT

Drug Facts__________________________________________________________________________________________________________

HPUS active ingredients: Baptisia tinctoria, Calcarea fluorica, Causticum, Hepar sulphuris calcareum, Hypericum perforatum, Ignatia amara, Kalmia latifolia, Nux vomica, Phytolacca decandra, Rhus toxicodendron, Sanguinaria canadensis, Symphytum officinale. Equal volumes of each ingredient in 10X, 30X, and LM1 potencies.

INDICATIONS AND USAGE

Uses for temporary relief of: facial pains of the jaw, facial neuralgia, rigid jaw muscles, inflammation in the jaw, clenching of the jaw, cracking sounds.

Inactive Ingredients:

Bio-Energetically Enhanced™ pure water, citric acid and potassium sorbate.

Warnings

- Stop use and ask your doctor if symptoms persist or worsen.
- If pregnant or breast-feeding, ask a healthcare professional before ues.

- Keep out of reach of children.

Directions

- Initially, depress pump until primed.
- Spray one dose directly into mouth.
- Ages 12 and up: 3 sprays 3 times per day.
- Ages 2-12: 2 sprays 3 times per day

OTHER SAFETY INFORMATION

Tamper resistant for your protection. Use only if safety seal is intact.

PURPOSE

Uses for temporary relief of:

- facial pains of the jaw
- facial neuralgia
- rigid jaw muscles
- inflammation in the jaw
- clenching of the jaw
- cracking sounds